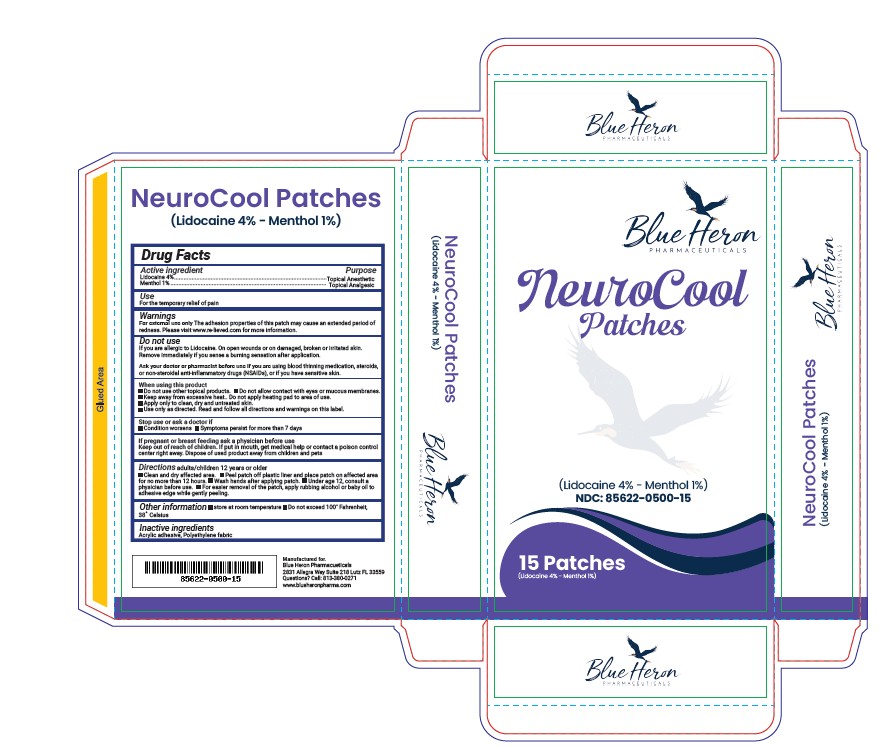 DRUG LABEL: NeuroCool Patches
NDC: 85622-500 | Form: PATCH
Manufacturer: Blue Heron Pharmaceuticals LLC
Category: otc | Type: HUMAN OTC DRUG LABEL
Date: 20251216

ACTIVE INGREDIENTS: LIDOCAINE 4 mg/100 mg; MENTHOL 1 mg/100 mg
INACTIVE INGREDIENTS: ACRYLIC ACID

NeuroCool

Active Ingredients

Lidocaine 4%

Menthol 1%

Purposes

Topical analgesic

Uses

For the temporary relief of pain

Warnings

For external use only

Do Not Use

- If you are allergic to Lidocaine or Menthol
- On open wounds or on damaged, broken or irritated skin
- Remove immediately if you sense a burning sensation after application

When using this product:

- Do not use other topical products.
- Do not allow contact with eyes or mucous membranes
- Keep away from excessive heat.
- Do not apply heating pad to area of use.
- Apply only to clean, dry, untreated skin.
- Use only as directed. Read and follow all directions and warnings on this label.

Stop use and ask a doctor if:

- Condition worsens
- Symptoms persist for more than 7 days

If pregnant or breast-feeding,

Ask a physician before use.

Keep out of reach of children

If put in mouth, get medical help or contact a poison control center right away. Dispose of used product away from children and pets.

Directions

Adult and children 12 years of age and over:

- Clean and dry affected area
- Peel patch off plastic liner and place patch on affected area for no more than 12 hours
- Wash hands after applying patch
- Under age 12, consult a physician before use
- For easier removal of the patch, apply rubbing alcohol or baby oil to adhesive edge while gently peeling

Children under 12 years of age: Consult a doctor

Storage

- Store at 68-77℉ (20-25℃) - Room Temperature
- Do not exceed 100oF (38oC)

Inactive Ingredients

Acrylic Adhesive, Polyethylene Fabric

Questions?

Call: 813-380-0271